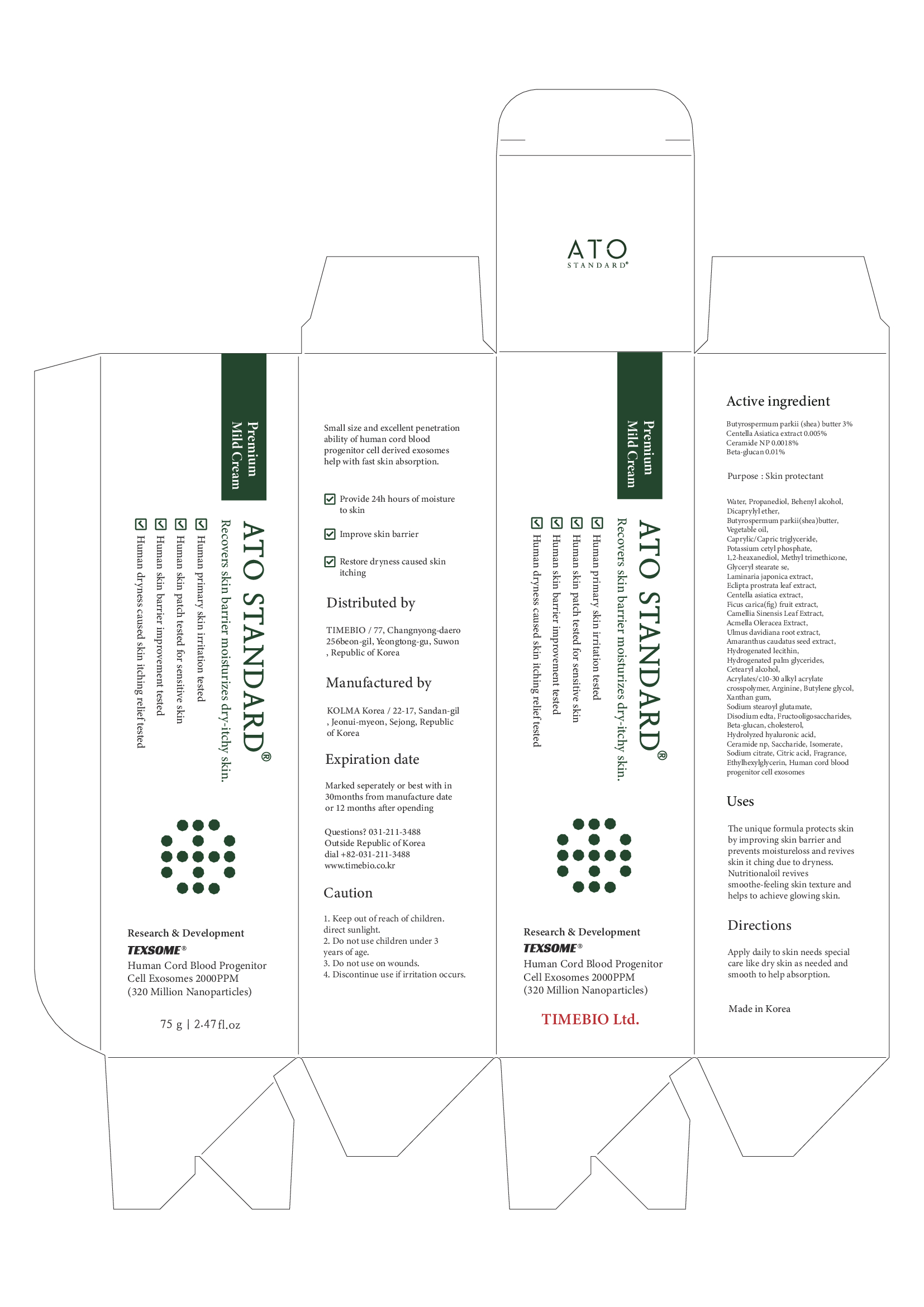 DRUG LABEL: ATO STANDARD PREMIUM MILDCREAM
NDC: 81160-201 | Form: CREAM
Manufacturer: TIMEBIO Co., Ltd
Category: otc | Type: HUMAN OTC DRUG LABEL
Date: 20211117

ACTIVE INGREDIENTS: CENTELLA ASIATICA WHOLE 0.005 g/100 g; SHEA BUTTER 3 g/100 g; CERAMIDE NP 0.0018 g/100 g
INACTIVE INGREDIENTS: DOCOSANOL; GLYCERYL STEARATE SE; ECLIPTA PROSTRATA LEAF; HYDROGENATED SOYBEAN LECITHIN; MEDIUM-CHAIN TRIGLYCERIDES; METHYL TRIMETHICONE; WATER; PROPANEDIOL; CORN OIL; POTASSIUM CETYL PHOSPHATE; LAMINARIA JAPONICA; FIG; CHOLESTEROL; AMARANTHUS CAUDATUS SEED; CETOSTEARYL ALCOHOL; SODIUM STEAROYL GLUTAMATE; EDETATE DISODIUM ANHYDROUS; SODIUM CITRATE, UNSPECIFIED FORM; GREEN TEA LEAF; ACMELLA OLERACEA FLOWERING TOP; HYDROGENATED PALM GLYCERIDES; XANTHAN GUM; CITRIC ACID MONOHYDRATE; ETHYLHEXYLGLYCERIN; BUTYLENE GLYCOL; DICAPRYLYL ETHER; 1,2-HEXANEDIOL; ULMUS DAVIDIANA ROOT; CARBOMER INTERPOLYMER TYPE A (ALLYL SUCROSE CROSSLINKED); ARGININE; SACCHARIDE ISOMERATE

81160-201 ATO STANDARD Premium Mild Cream

Active Ingredient

BUTYROSPERMUM PARKII (SHEA) BUTTER 3%

CENTELLA ASIATICA EXTRACT 0.005%

CERAMIDE NP 0.0018%

BETA-GLUCAN 0.01%

Purpose

Skin protectant

Uses

The unique formula protects skin by improving skin barrier and prevents moistureloss and revives skin itching due to dryness.

Nutritional oil revives smoothe-feeling skin texture and helps to achieve glowing skin.

Warnings

Direct sunlight.

Do not use children under 3 years of age

Do not use on wounds

Warnings

Discontinue use if irritation occurs.

Warnings

Keep out of reach of children.

Directions

Apply daily to skin needs special care like dry skin as needed and smooth to help absorption.

Inactive Ingredient

WATER, PROPANEDIOL, BEHENYL ALCOHOL, DICAPRYLYL ETHER, VEGETABLE OIL, CAPRYLIC/CAPRIC TRIGLYCERIDE, POTASSIUM CETYL PHOSPHATE, 1,2-HEXANEDIOL, METHYL TRIMETHICONE, GLYCERYL STEARATE SE, LAMINARIA JAPONICA EXTRACT, ECLIPTA PROSTRATA LEAF EXTRACT, FICUS CARICA (FIG) FRUIT EXTRACT, CAMELLIA SINENSIS LEAF EXTRACT, ACMELLA OLERACEA EXTRACT, ULMUS DAVIDIANA ROOT EXTRACT, AMARANTHUS CAUDATUS SEED EXTRACT, HYDROGENATED LECITHIN, WATER (and) HUMAN CORD BLOOD PROGENITOR CELL EXOSOMES, HYDROGENATED PALM GLYCERIDES, CETEARYL ALCOHOL, ACRYLATES/C10-30 ALKYL ACRYLATE CROSSPOLYMER, ARGININE, BUTYLENE GLYCOL, XANTHAN GUM, SODIUM STEAROYL GLUTAMATE, DISODIUM EDTA,FRUCTOOLIGOSACCHARIDES, BETA-GLUCAN, CHOLESTEROL, HYDROLYZED HYALURONIC ACID, SACCHARIDE ISOMERATE, SODIUM CITRATE, CITRIC ACID, FRAGRANCE, ETHYLHEXYLGLYCERIN